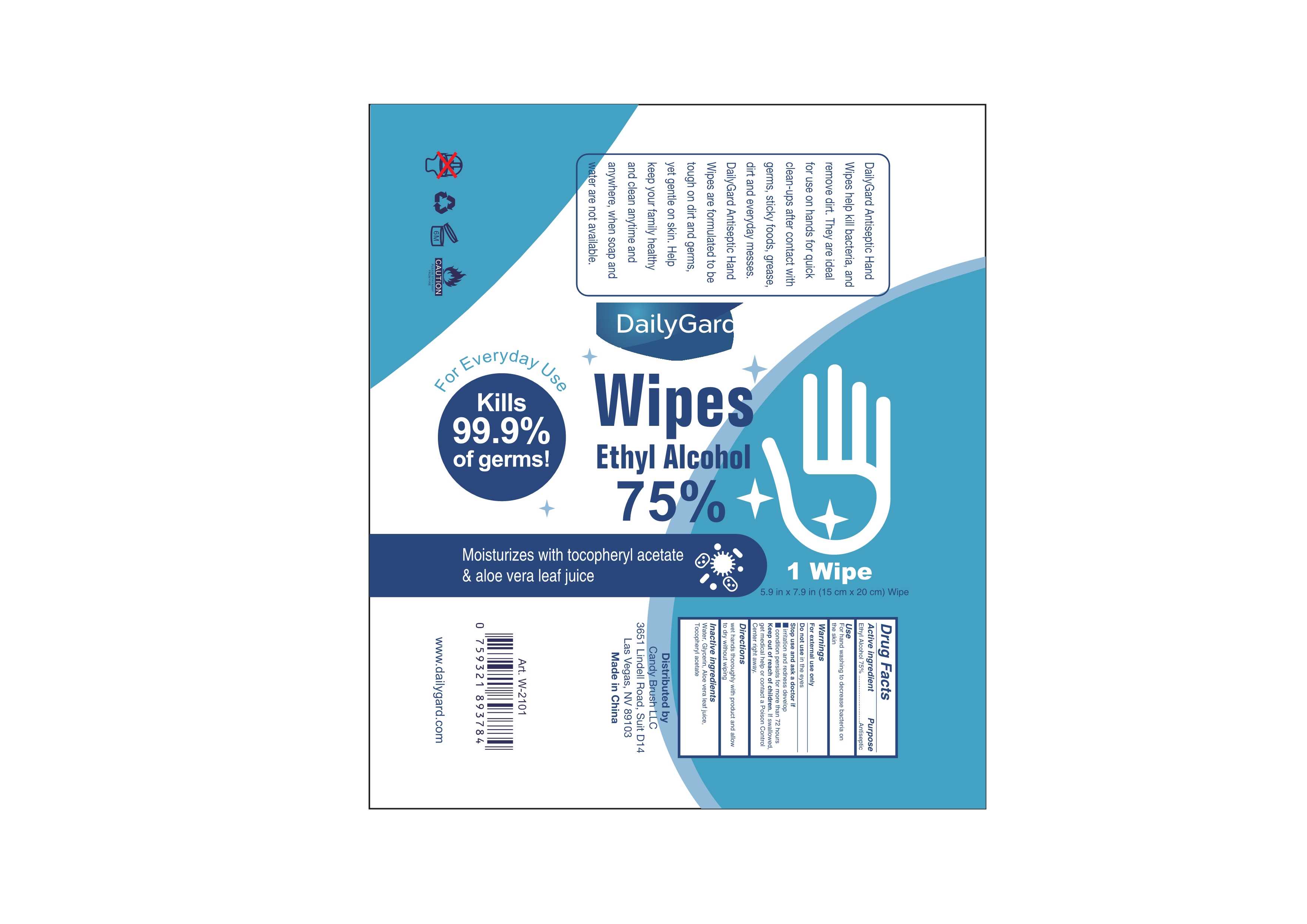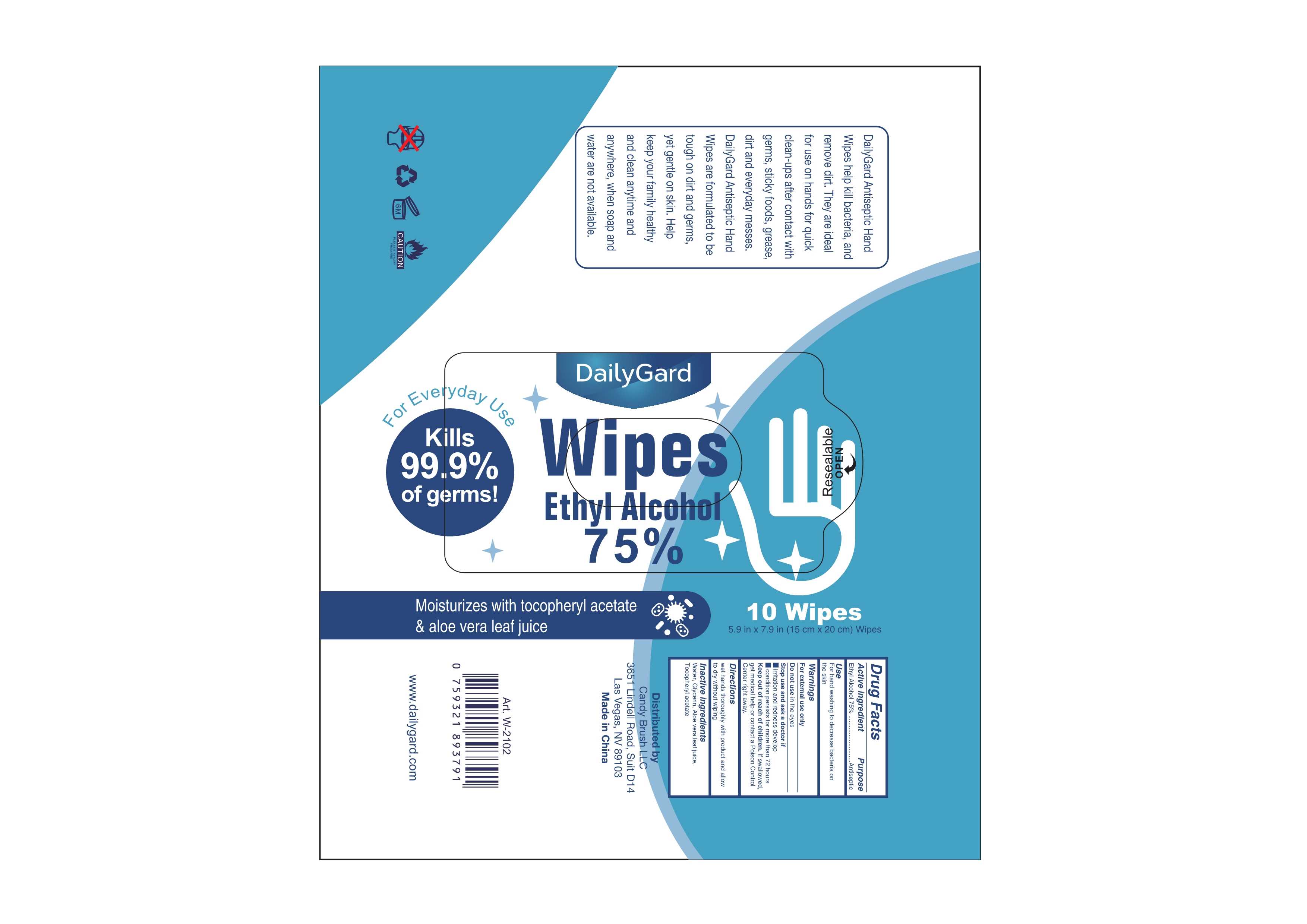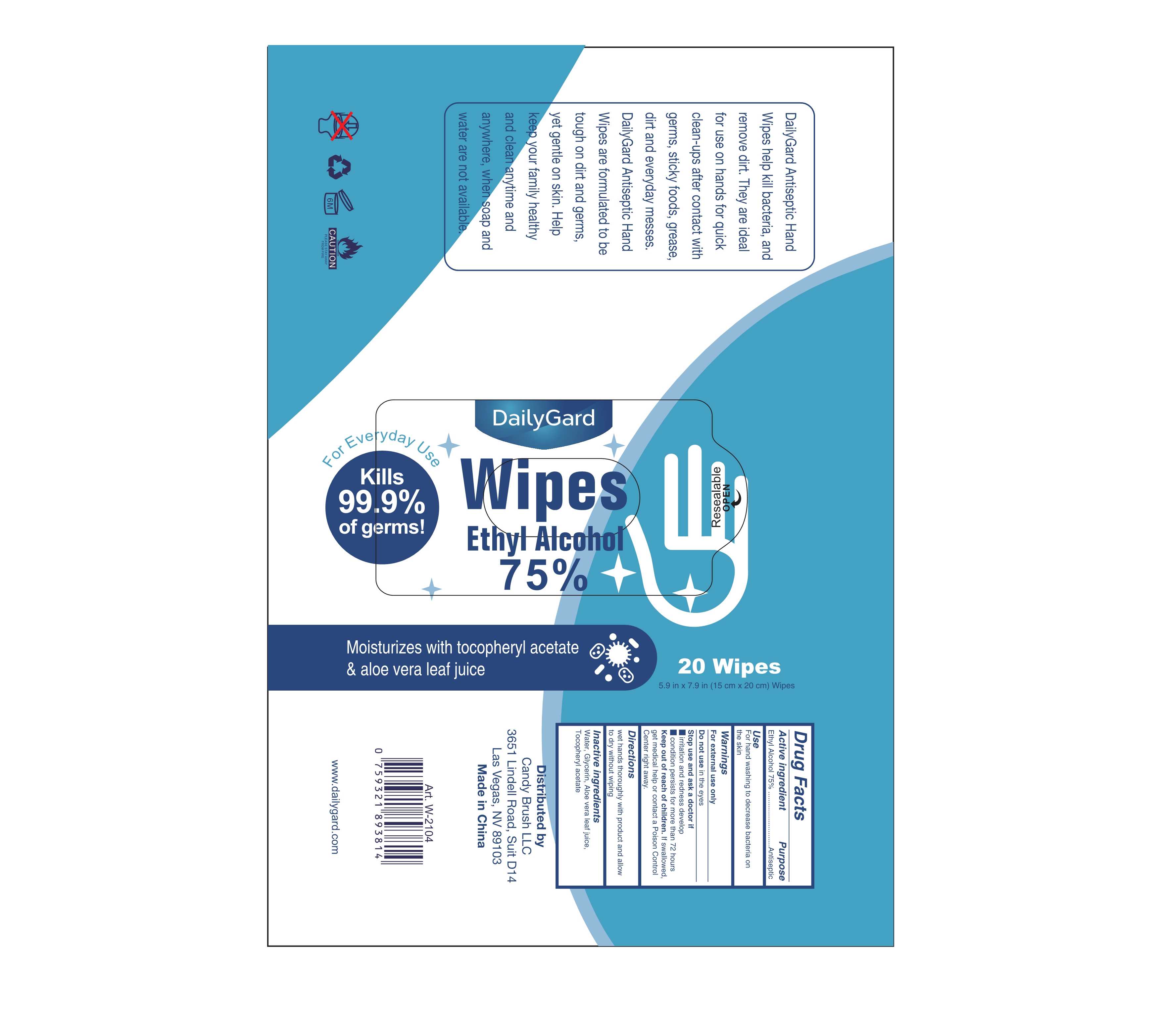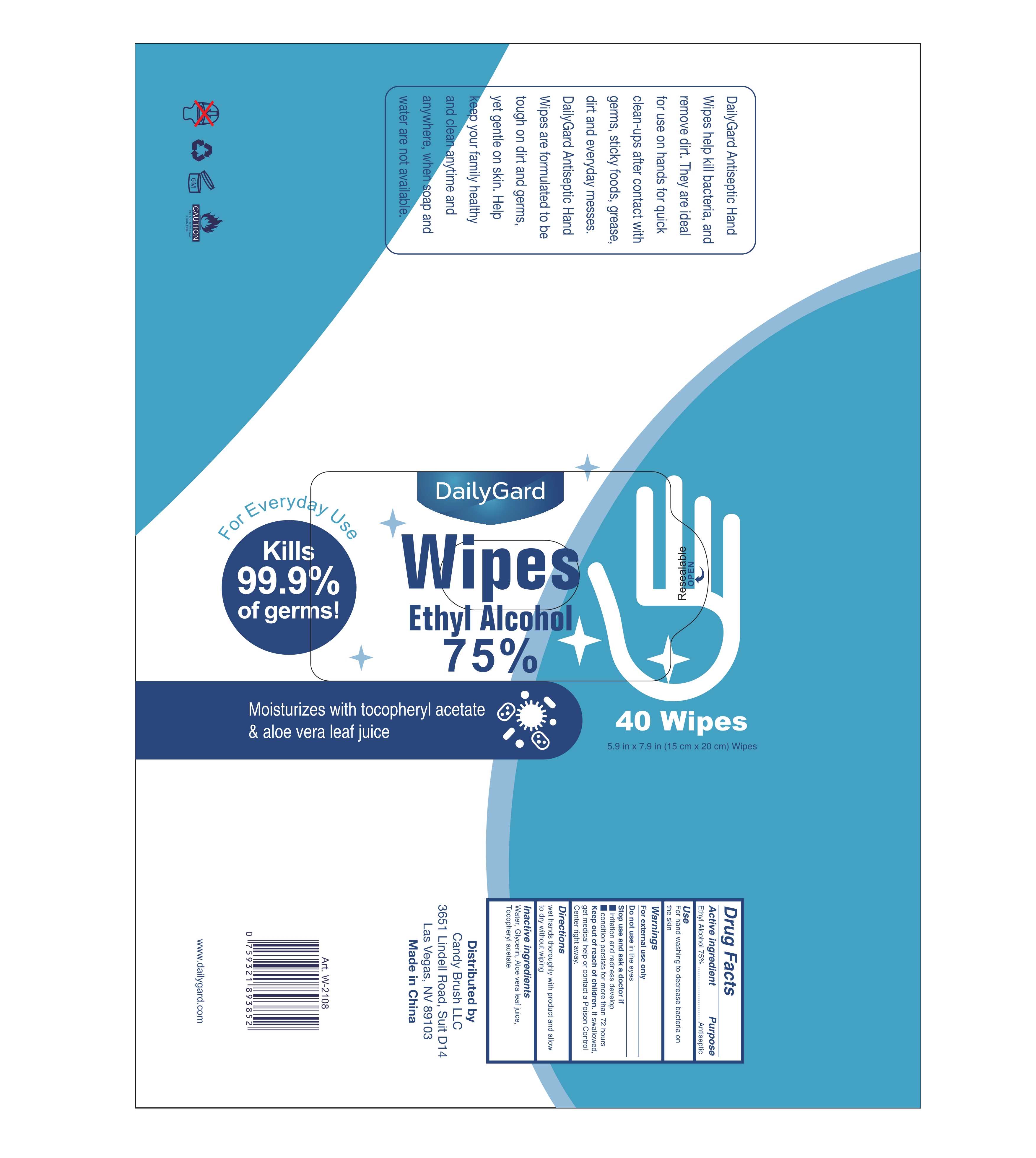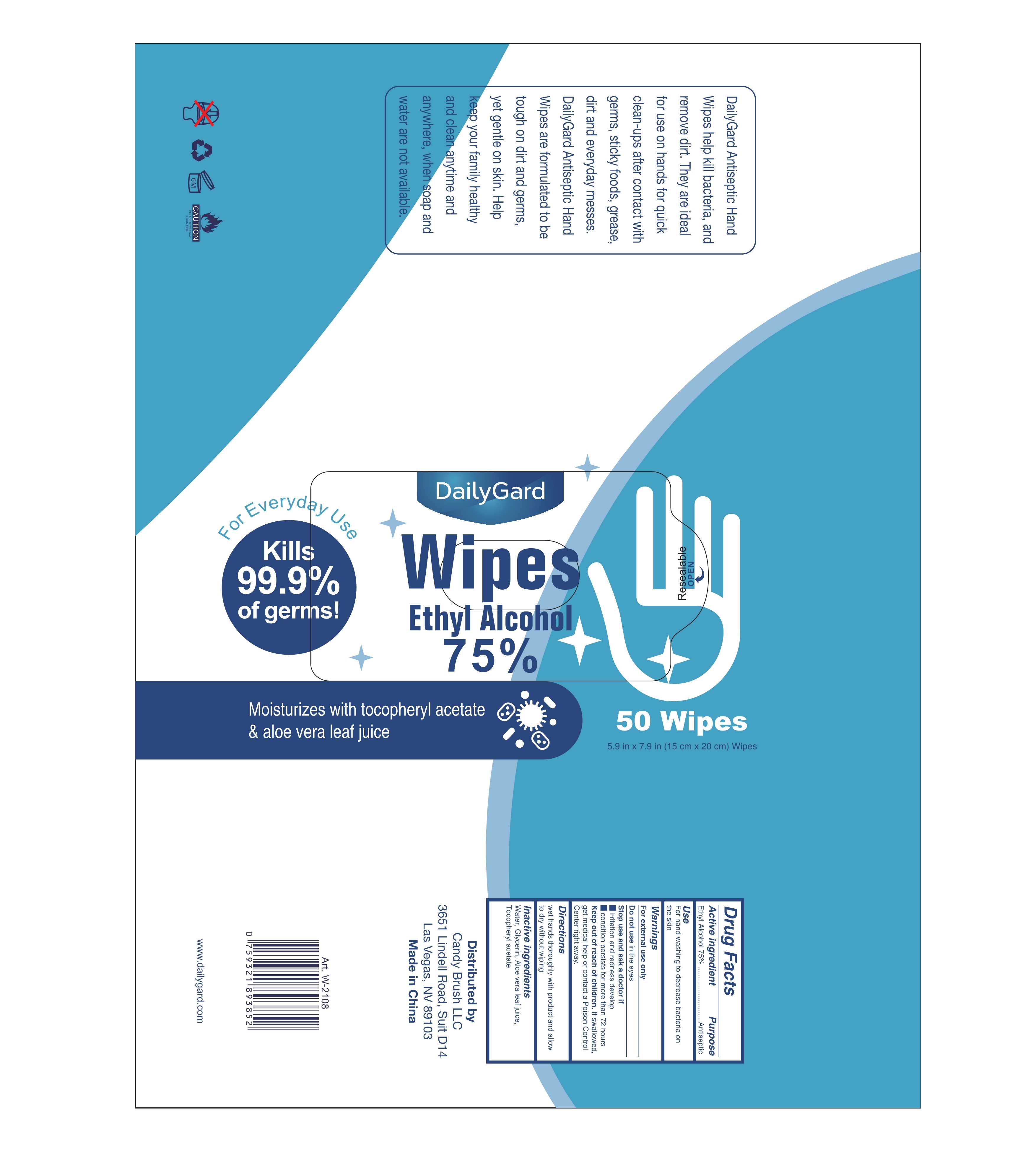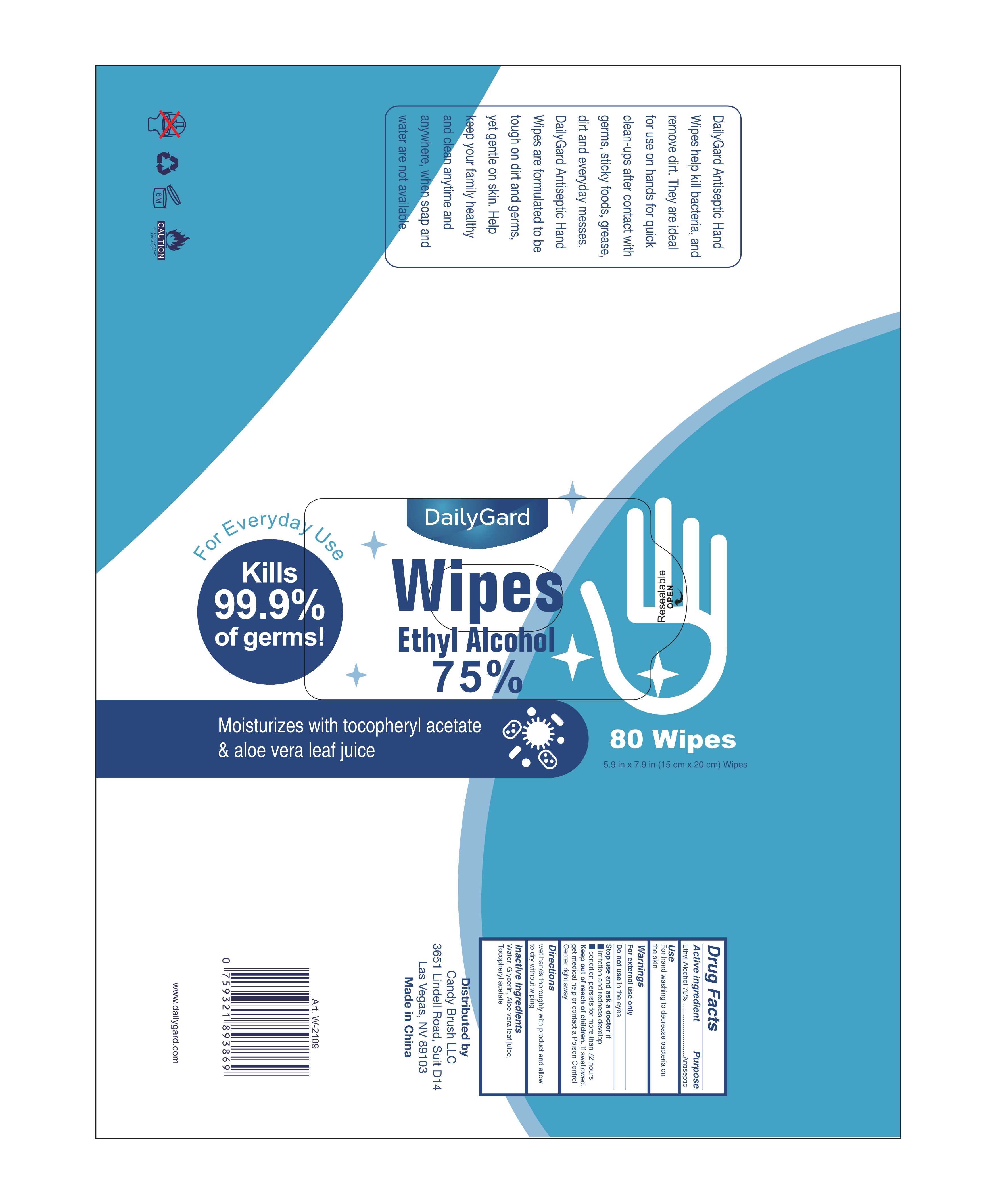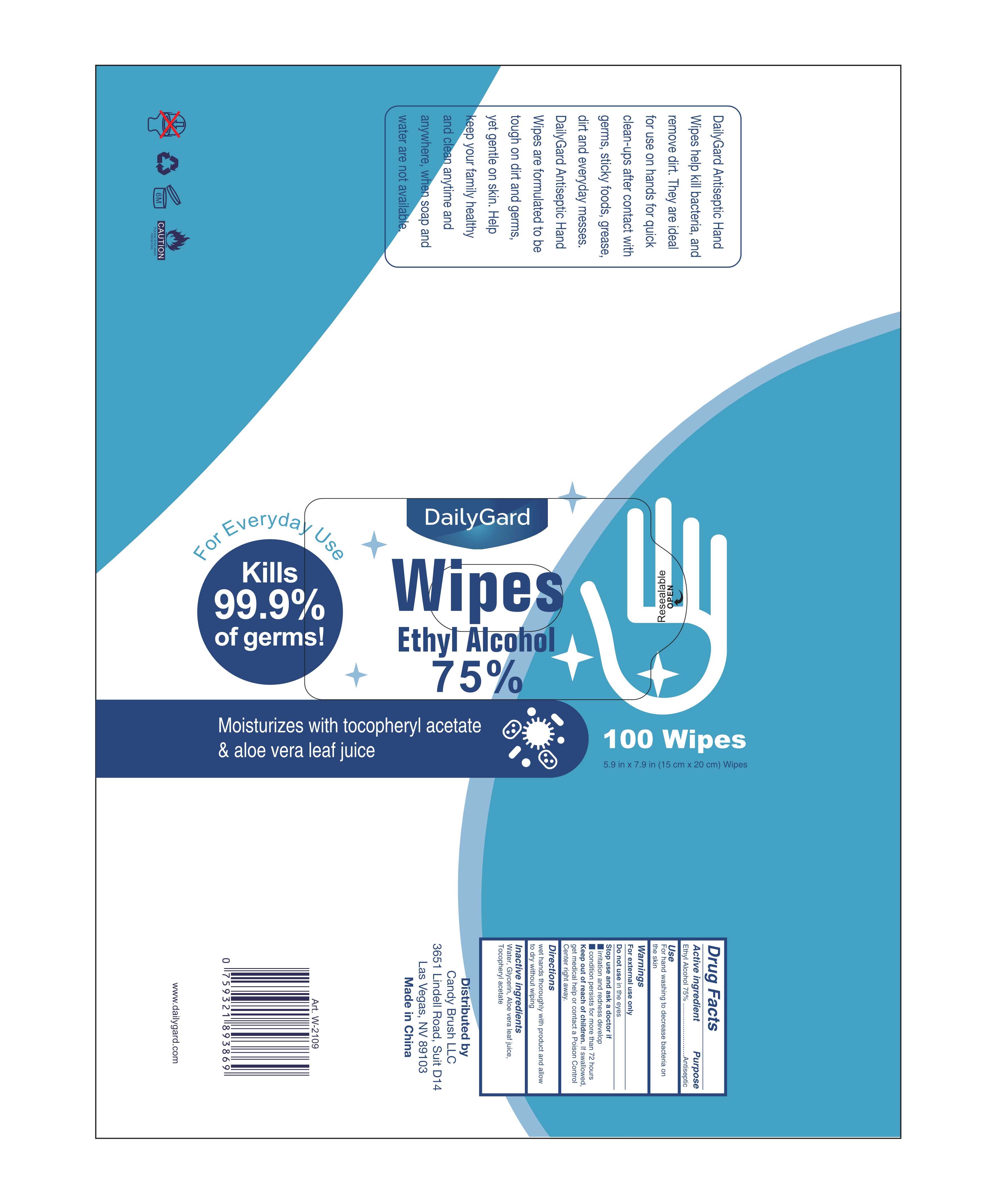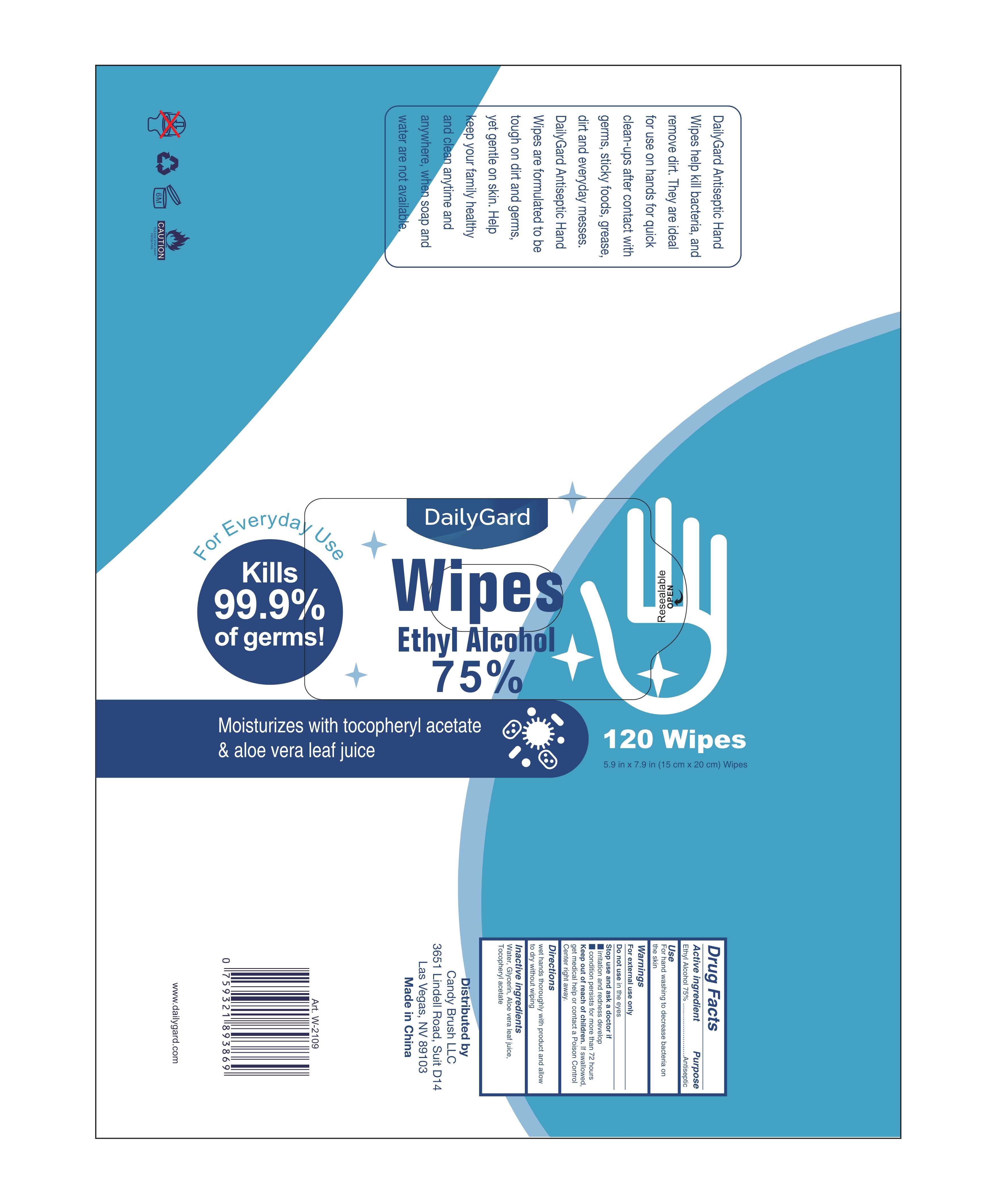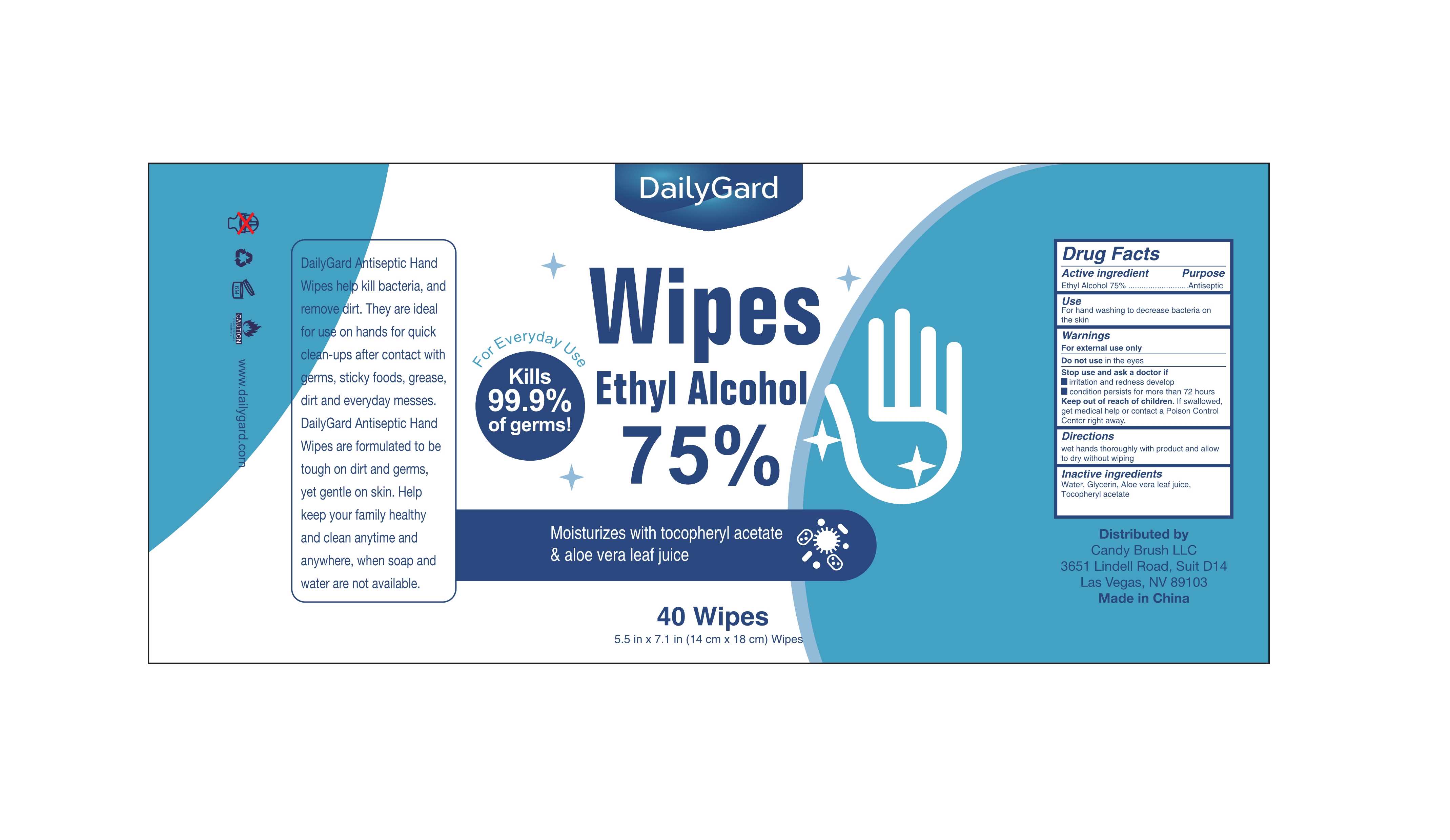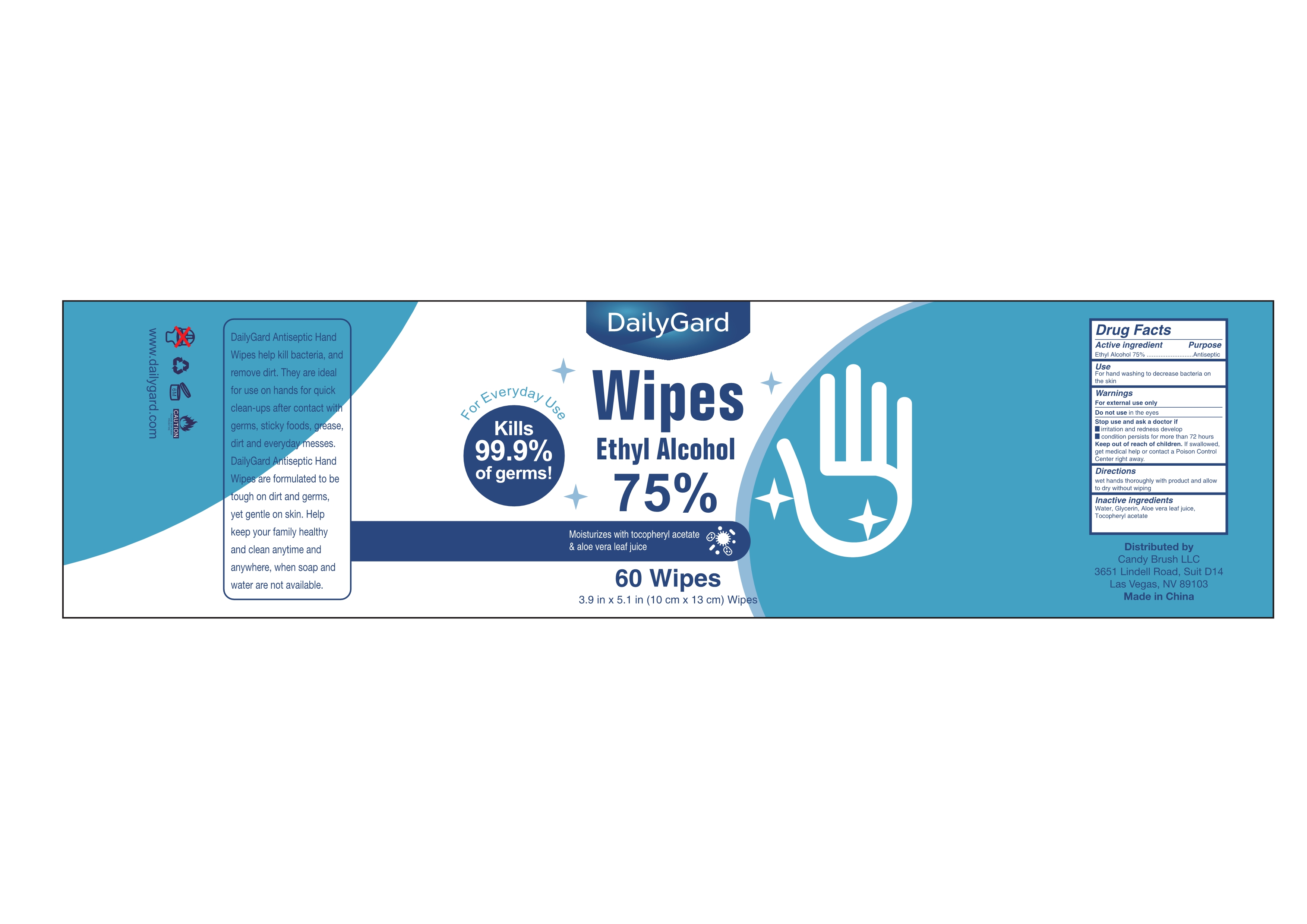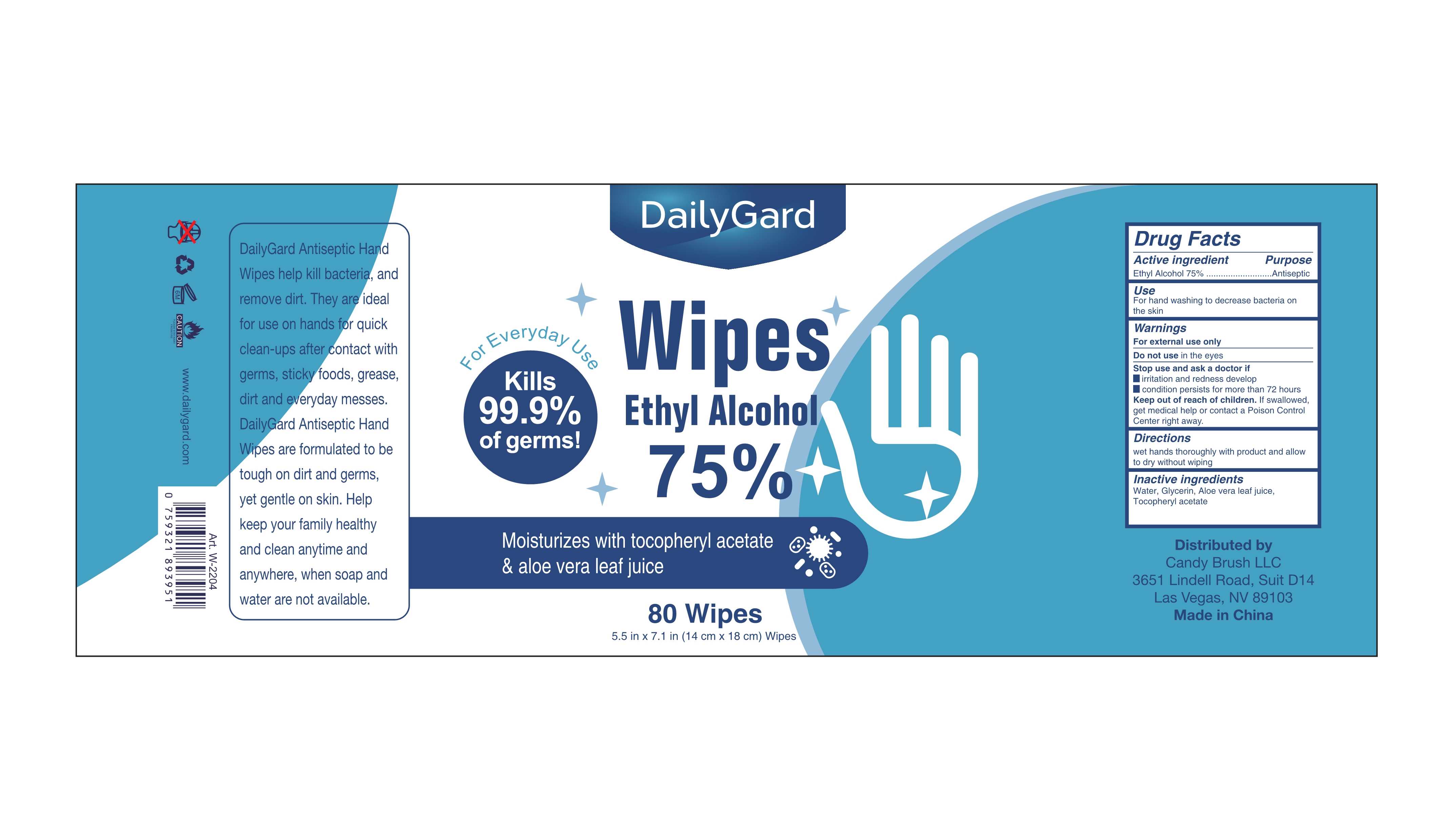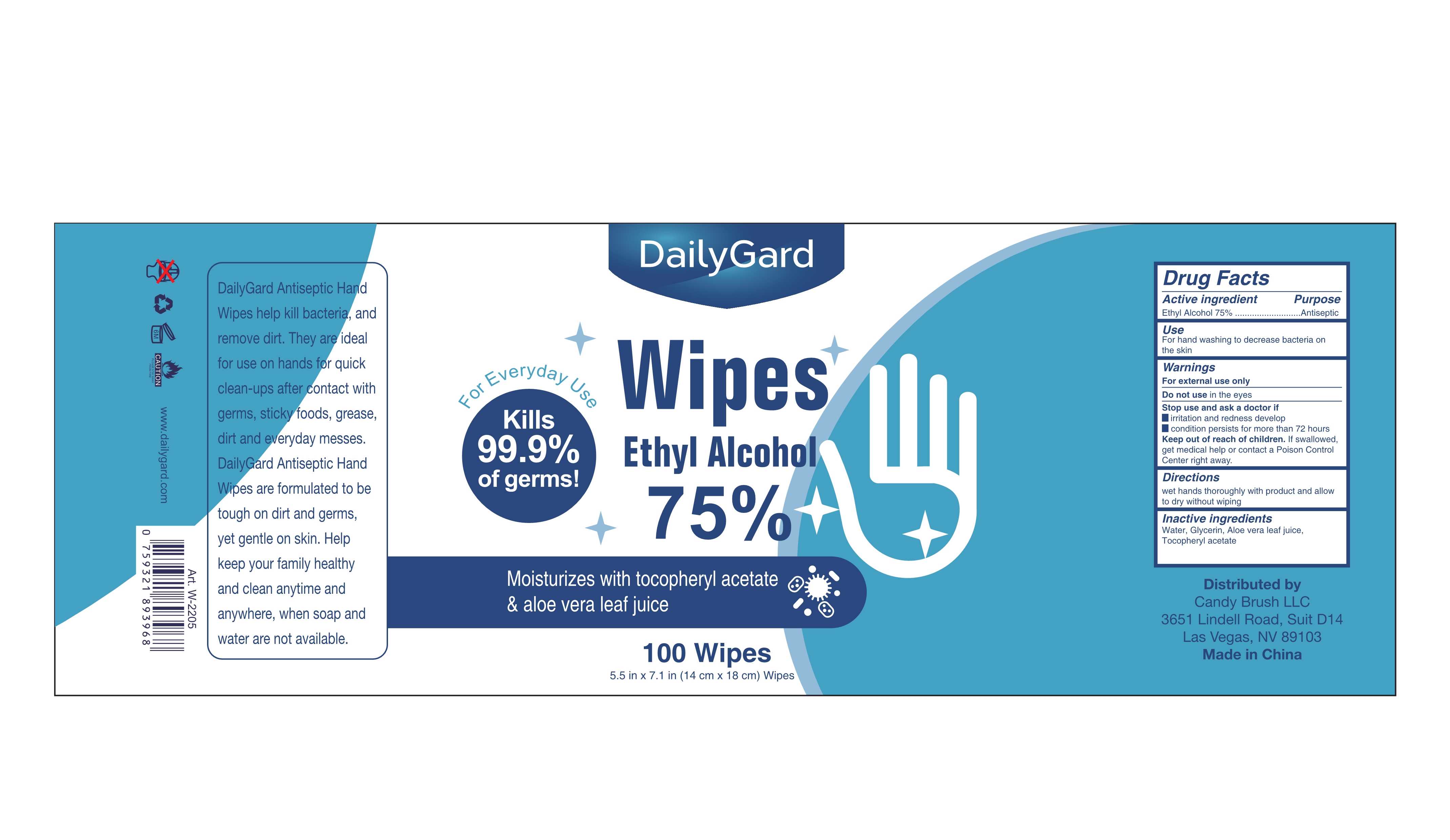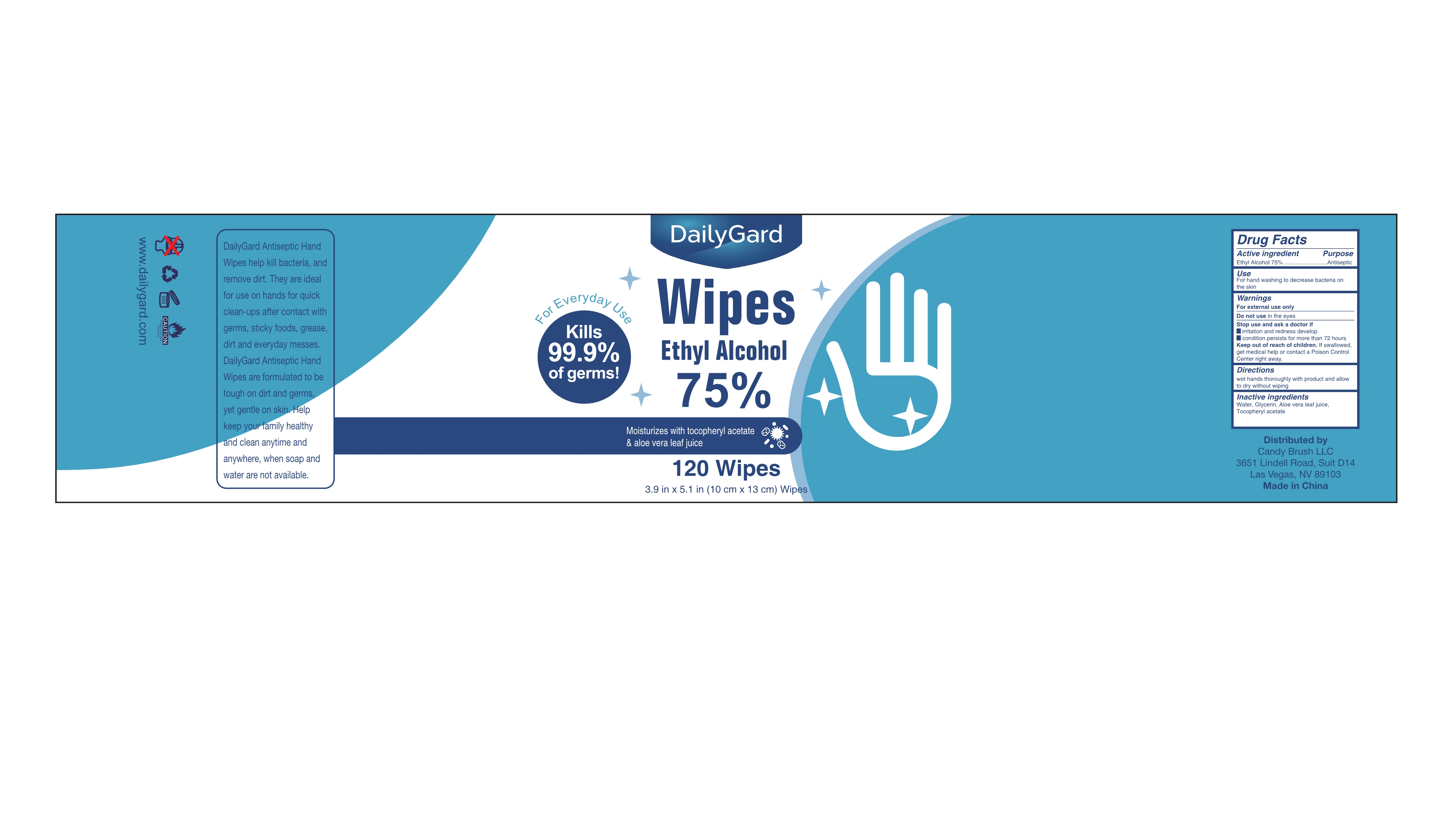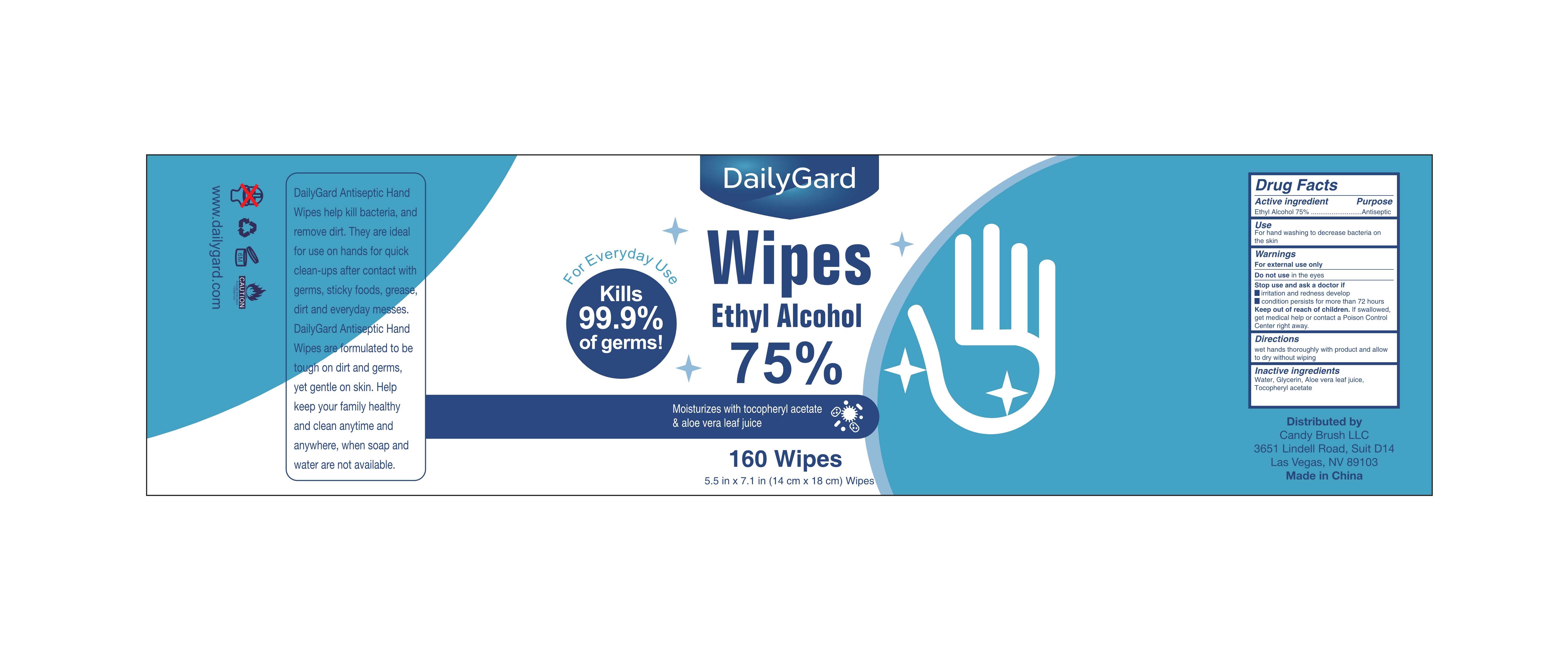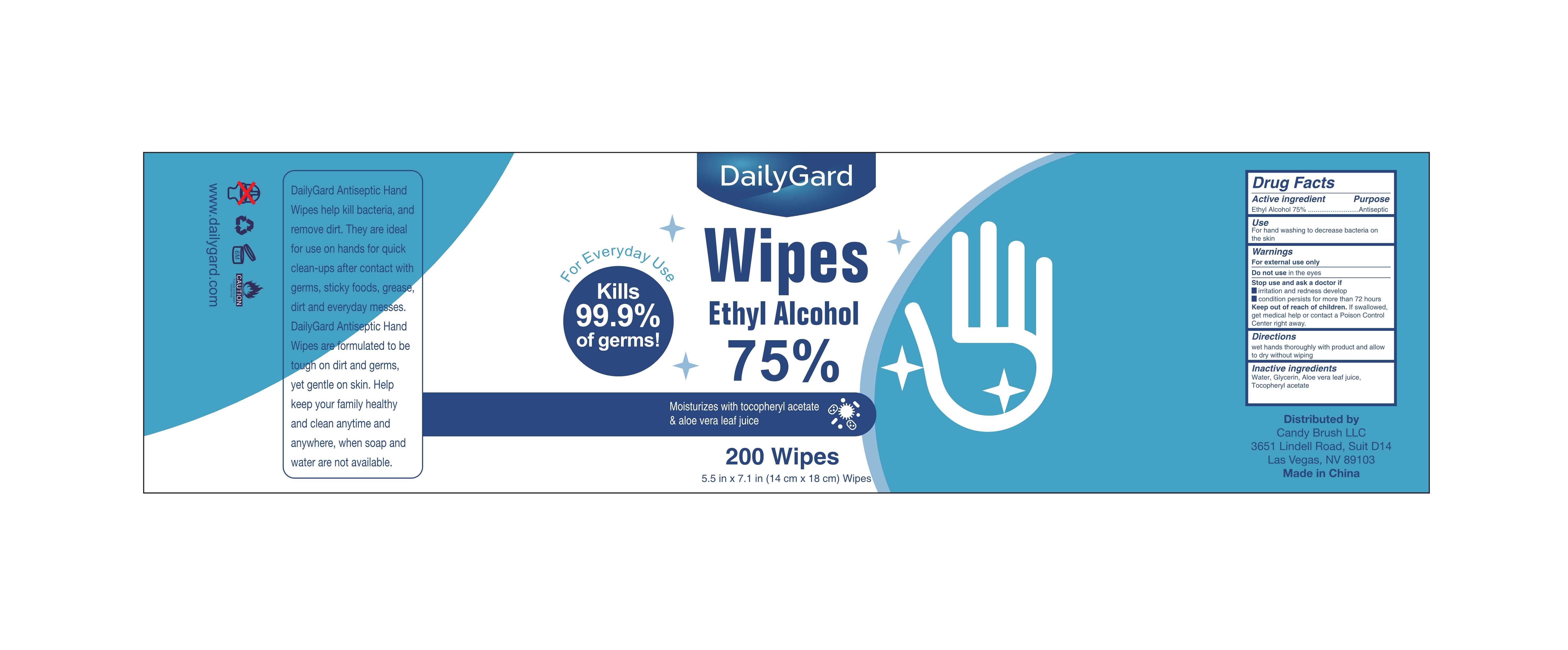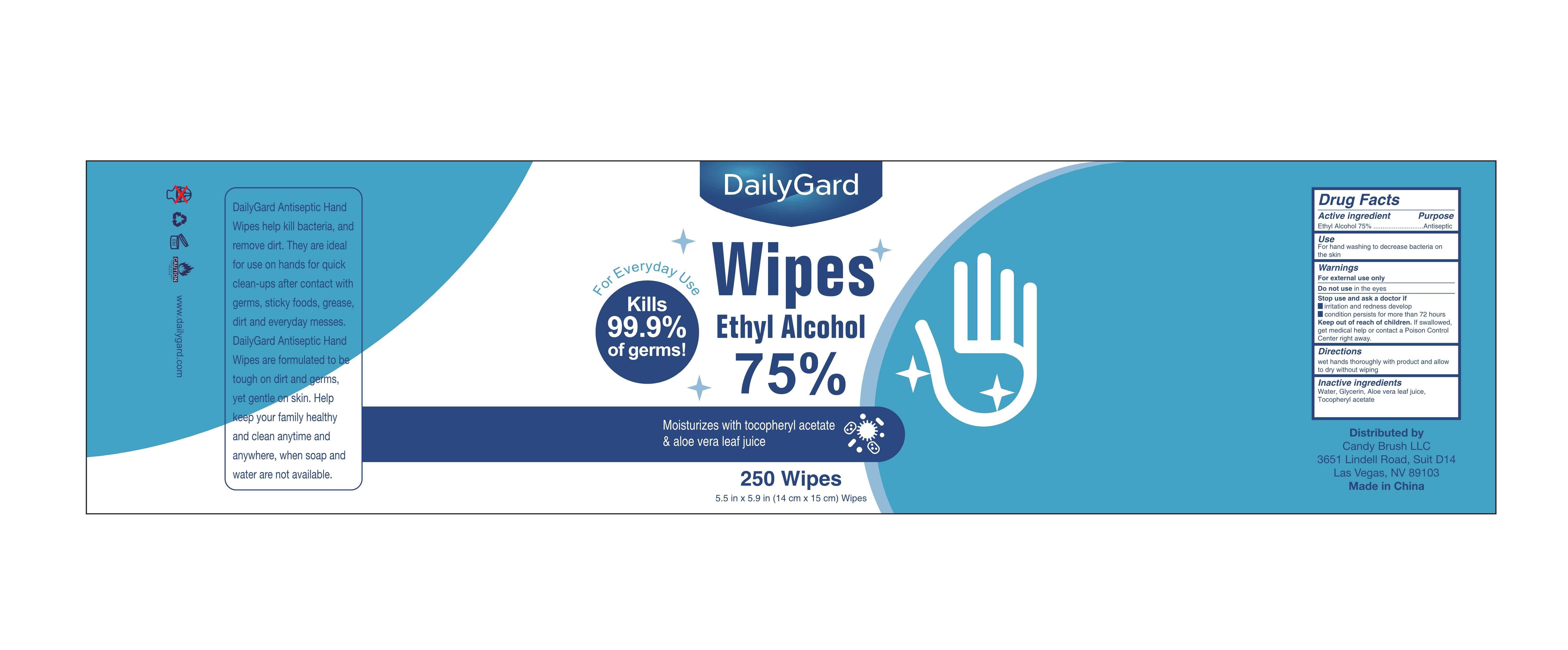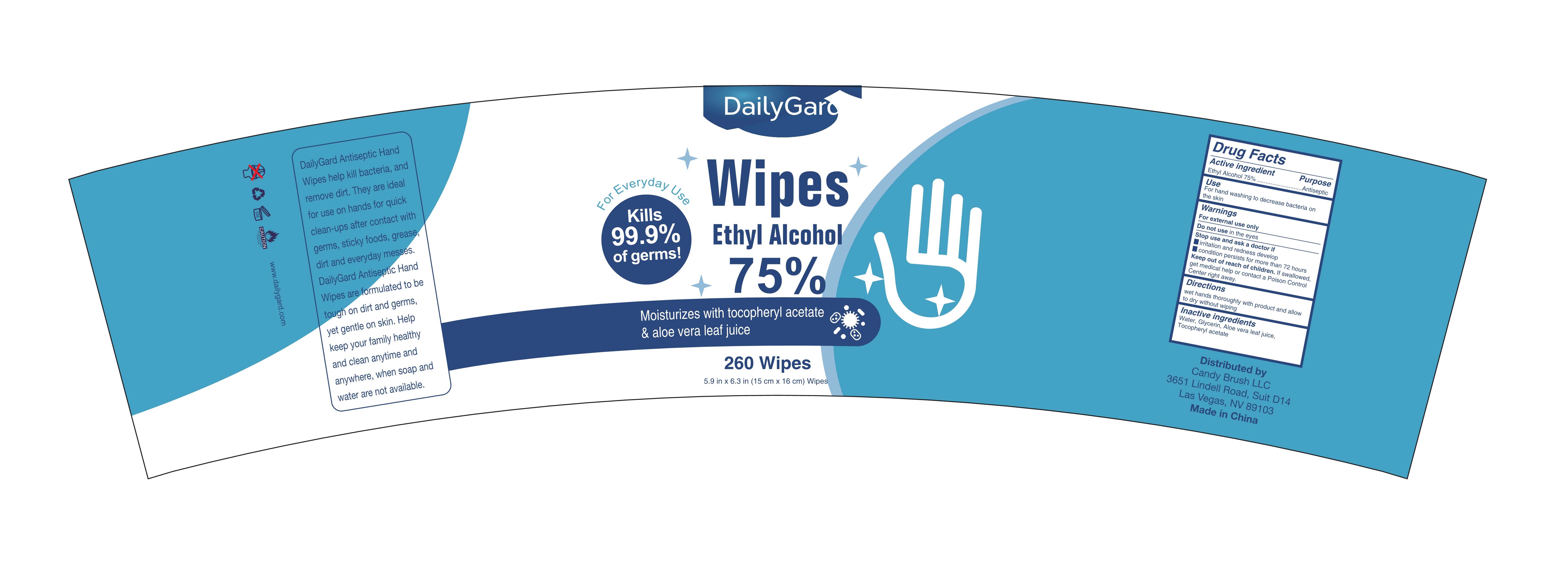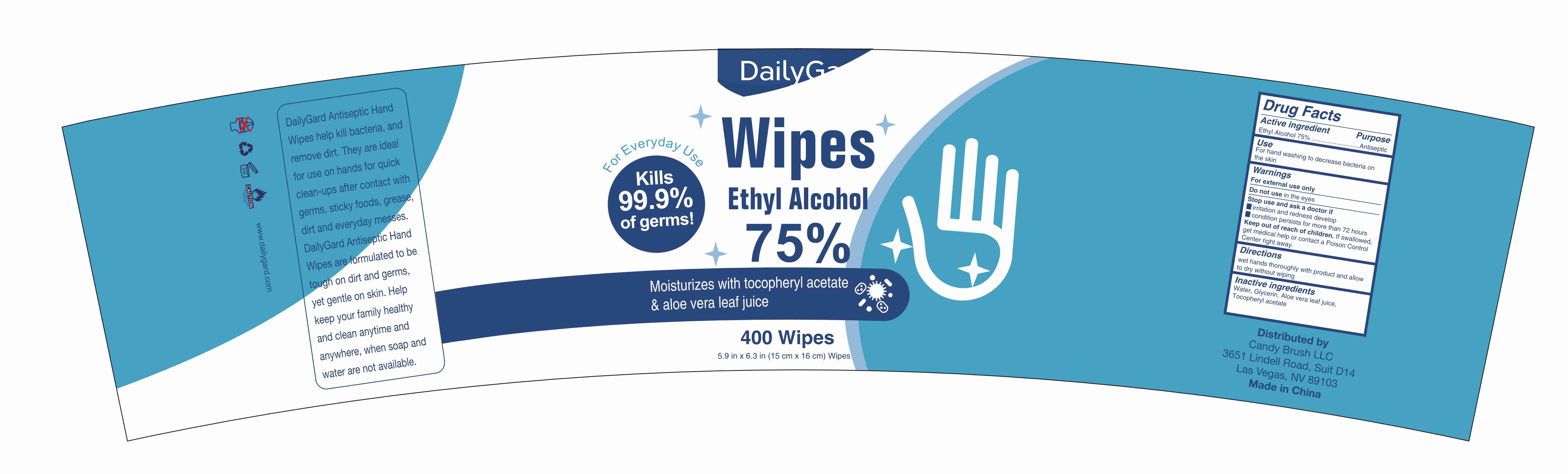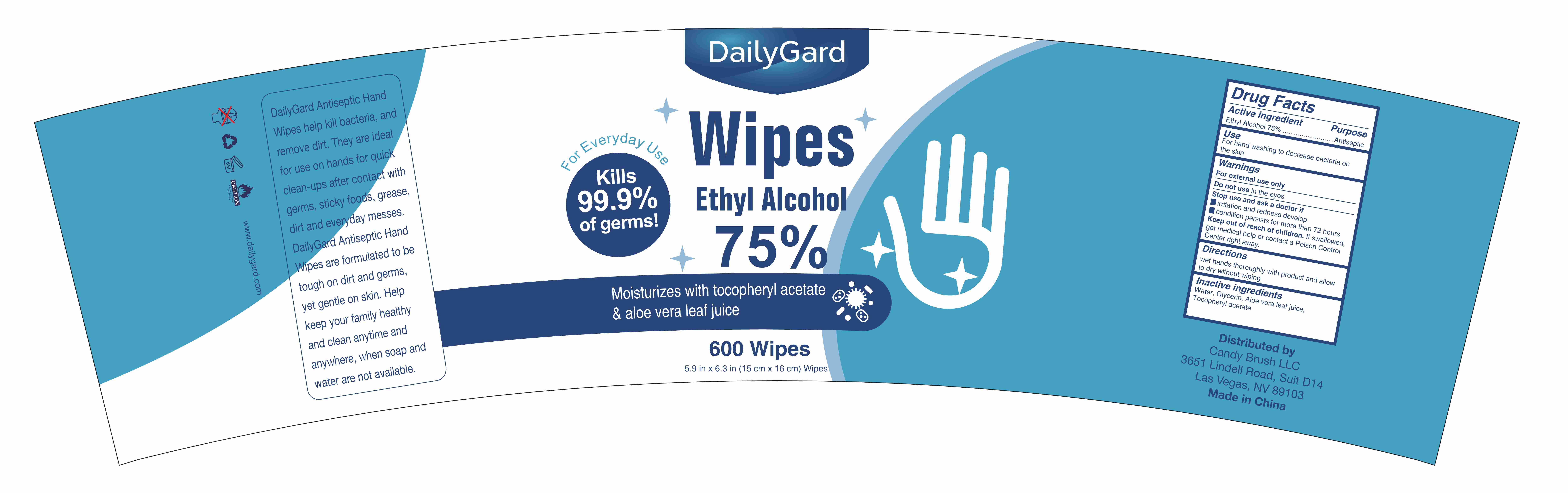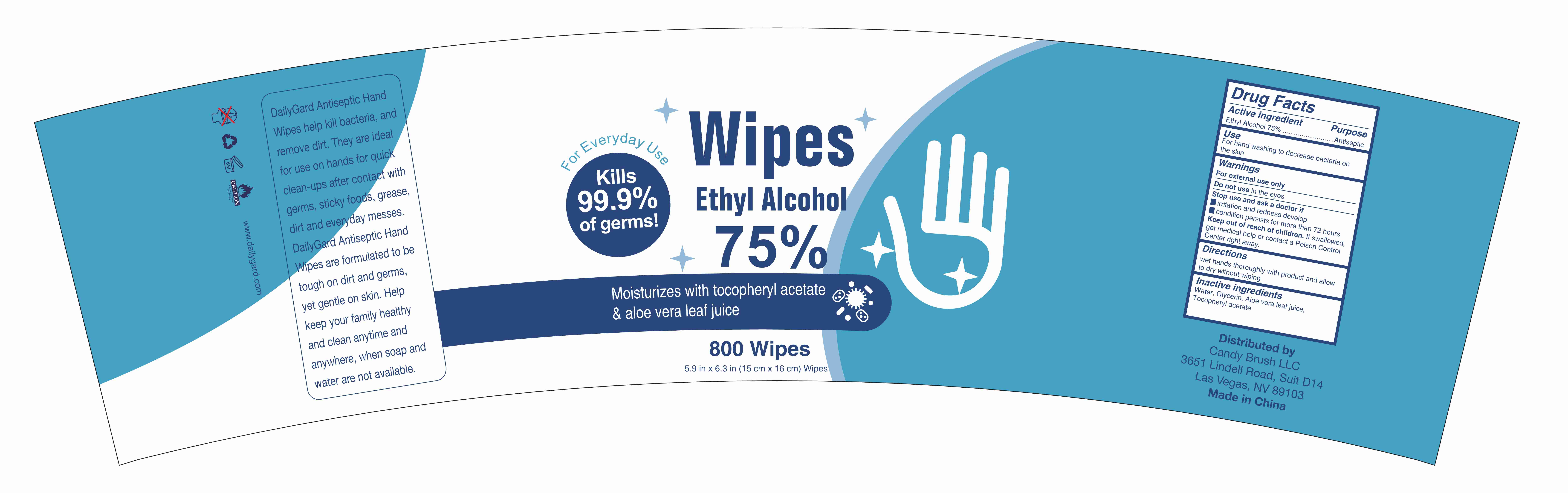 DRUG LABEL: Ethy Alcohol Wipes
NDC: 80110-015 | Form: CLOTH
Manufacturer: Anhui Germaphob Daily Commodity Co., Ltd.
Category: otc | Type: HUMAN OTC DRUG LABEL
Date: 20210222

ACTIVE INGREDIENTS: ALCOHOL 75 mL/100 1
INACTIVE INGREDIENTS: .ALPHA.-TOCOPHEROL ACETATE; GLYCERIN; ALOE VERA LEAF; WATER

013 changed to 015
Ethy Alcohol Wipes

Active Ingredient(s)

Ethyl Alcohol75%

Purpose

Antibacterial

Use

For hand washing to decrease bacteria on the skin

Warnings

For external use only

Do not use in the eyes

Stop use and ask a doctor if
irritation and redness develop
condition persists for more than 72 hours

Keep out of reach of children. If swallowed, get medical help or contact a Poison Control Center right away.

Do not use in the eyes

When using this product Stop use and ask a doctor if
irritation and redness develop
condition persists for more than 72 hours

Keep out of reach of children. If swallowed, get medical help or contact a Poison Control Center right away.

Stop use and ask a doctor if
irritation and redness develop
condition persists for more than 72 hours

Keep out of reach of children. If swallowed, get medical help or contact a Poison Control Center right away.

Directions

wet hands thoroughly with product and allow to dry without wiping

Other information

/

Inactive ingredients

Water, Glycerin, Aloe barbadensis leaf juice, Tocopheryl acetate